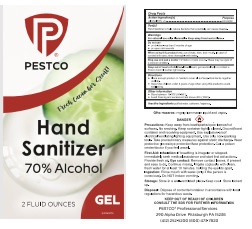 DRUG LABEL: Hand Sanitizer
NDC: 82039-010 | Form: GEL
Manufacturer: Pestco Professional Services, LLC
Category: otc | Type: HUMAN OTC DRUG LABEL
Date: 20210617

ACTIVE INGREDIENTS: ALCOHOL 70 mL/100 mL
INACTIVE INGREDIENTS: TROLAMINE; CARBOMER HOMOPOLYMER, UNSPECIFIED TYPE; WATER; LINALOOL, (+)- 0.002 mL/100 mL; CYCLAMEN ALDEHYDE 0.004 mL/100 mL

Cucumber Hand Sanitizing Gel 70%

Active Ingredient(s)

Alcohol 70% v/v. Purpose: Antiseptic

Purpose

Antiseptic, Hand Sanitizer

Use

Hand Sanitizer to help reduce bacteria that potentially can cause disease.

Warnings

For external use only. Flammable. Keep away from heat or flame

Do not use

- in children less than 2 months of age
- on open skin wounds

When using this product keep out of eyes, ears, and mouth. In case of contact with eyes, rinse eyes thoroughly with water.
Stop use and ask a doctor if irritation or rash occurs. These may be signs of a serious condition.
Keep out of reach of children. If swallowed, get medical help or contact a Poison Control Center right away.

Stop use and ask a doctor if irritation or rash occurs. These may be signs of a serious condition.

Keep out of reach of children. If swallowed, get medical help or contact a Poison Control Center right away.

Directions

- Place enough product on hands to cover all surfaces. Rub hands together until dry.
- Supervise children under 6 years of age when using this product to avoid swallowing.

Other information

- Store between 15-30C (59-86F)
- Avoid freezing and excessive heat above 40C (104F)

Inactive ingredients

purified water USP, carbomer, fragrance

Package Label - Principal Display Panel

120 mL NDC: 82039-010-01